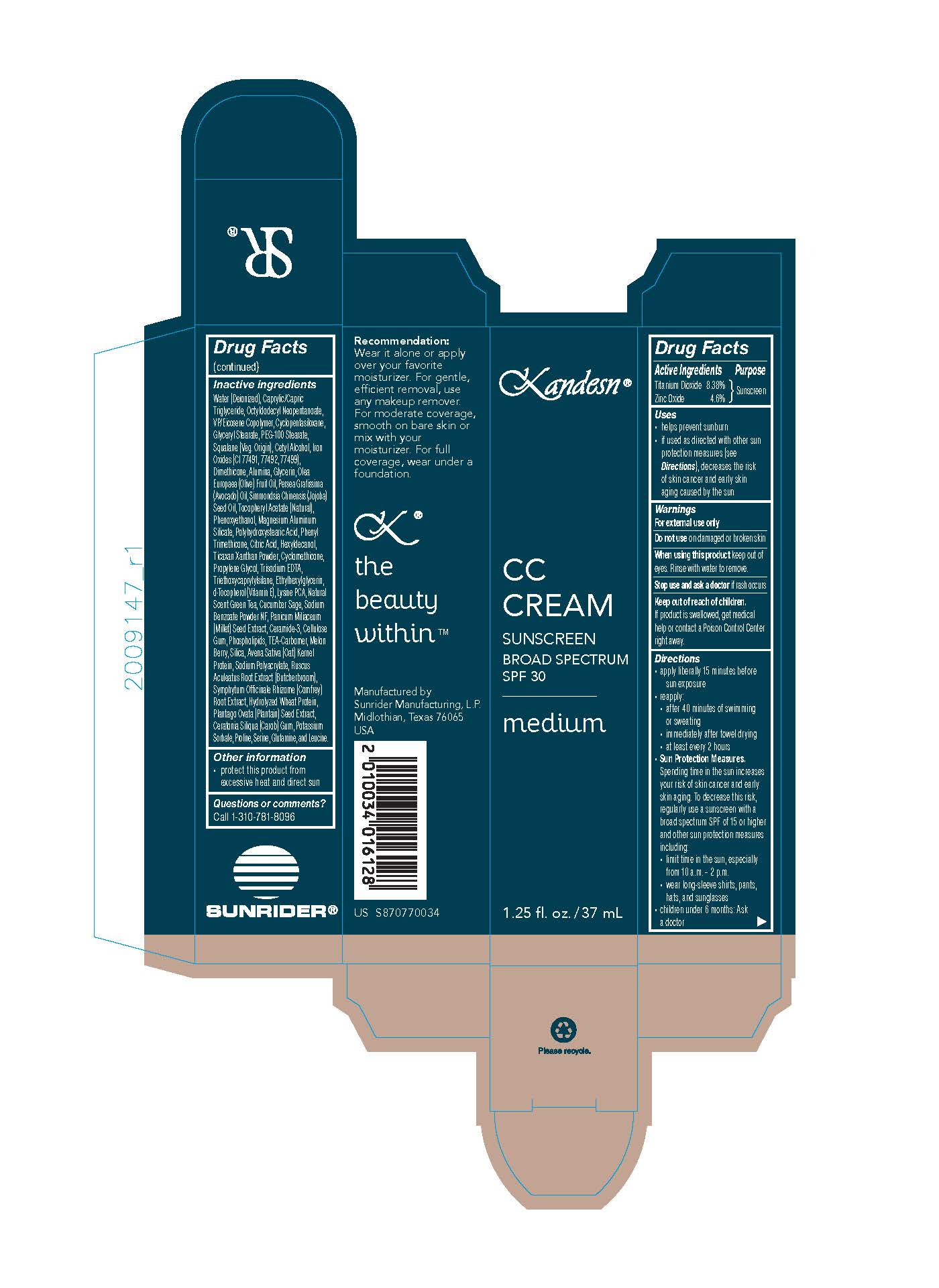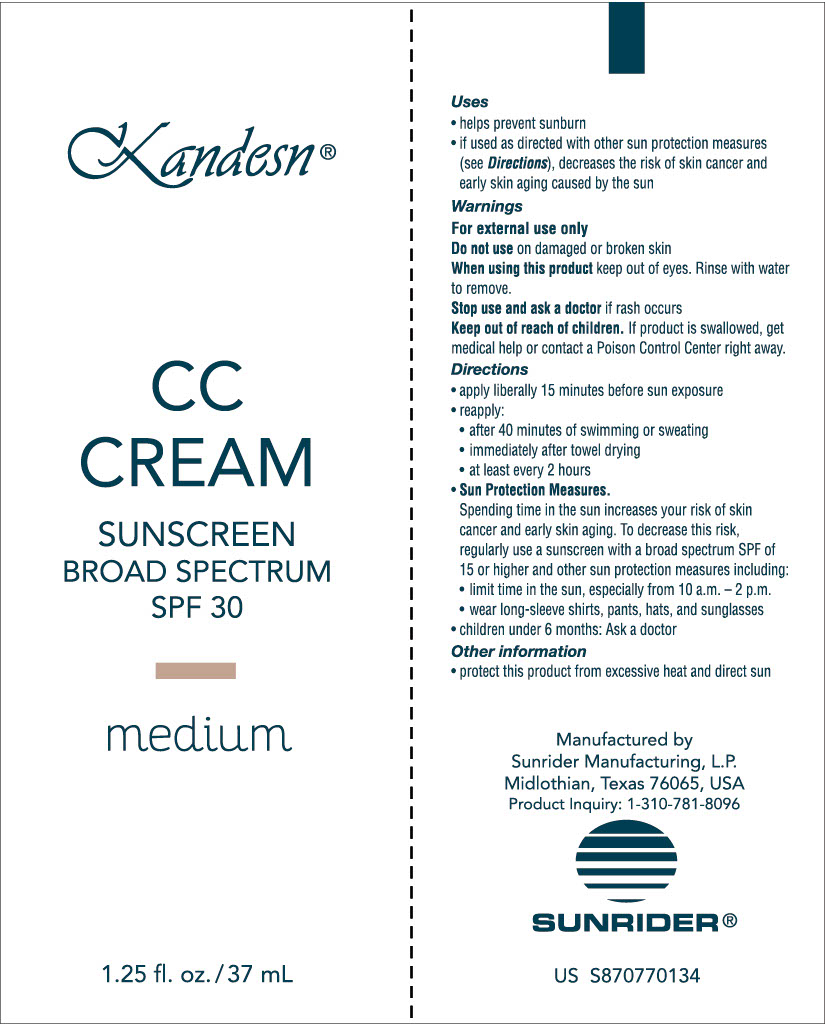 DRUG LABEL: Kandesn CC Cream
NDC: 62191-013 | Form: CREAM
Manufacturer: Sunrider Manufacturing L.P.
Category: otc | Type: HUMAN OTC DRUG LABEL
Date: 20251230

ACTIVE INGREDIENTS: TITANIUM DIOXIDE 114 mg/1 g; ZINC OXIDE 55 mg/1 g
INACTIVE INGREDIENTS: FERRIC OXIDE YELLOW; FERRIC OXIDE RED; PROLINE; WATER; CAPRYLIC/CAPRIC TRIGLYCERIDE; OCTYLDODECYL NEOPENTANOATE; VINYLPYRROLIDONE/EICOSENE COPOLYMER; CYCLOPENTASILOXANE; GLYCERYL STEARATE; PEG-100 STEARATE; SQUALANE; CETYL ALCOHOL; FERROSOFERRIC OXIDE; DIMETHICONE; ALUMINA; GLYCERIN; OLEA EUROPAEA (OLIVE) FRUIT OIL; PERSEA GRATISSIMA (AVOCADO) OIL; SIMMONDSIA CHINENSIS (JOJOBA) SEED OIL; ALPHA-TOCOPHEROL ACETATE; PHENOXYETHANOL; MAGNESIUM ALUMINUM SILICATE; POLYHYDROXYSTEARIC ACID (2300 MW); PHENYL TRIMETHICONE; CITRIC ACID; HEXYLDECANOL; XANTHAN GUM; CYCLOMETHICONE; PROPYLENE GLYCOL; TRISODIUM EDTA; TRIETHOXYCAPRYLYLSILANE; ETHYLHEXYLGLYCERIN; .DELTA.-TOCOPHEROL; LYSINE PCA; GREEN TEA LEAF; SAGE OIL; SODIUM BENZOATE; MILLET; CERAMIDE 3; CELLULOSE GUM; EGG PHOSPHOLIPIDS; CARBOMER; MELON; HYDRATED SILICA; OATMEAL; SODIUM POLYACRYLATE (2500000 MW); RUSCUS ACULEATUS ROOT; COMFREY ROOT; HYDROLYZED WHEAT PROTEIN (ENZYMATIC, 3000 MW); SERINE; LEUCINE; PLANTAGO OVATA SEED; POTASSIUM SORBATE; GLUTAMINE; CAROB

Kandesn CC Cream Medium

USES

- helps prevent sunburn
- if used as directed with other sun protection measures (see Directions), decreased the risk of skin cancer and early skin aging caused by the sun.

DIRECTIONS

- apply liberally 15 minutes before sun exposure
- Reapply:
- after 40 minutes of swimming or sweating
- immediately after towel drying
- at least every 2 hours
- Sun Protection Measures. Spending time in the sun increases your risk of skin cancer and early skin aging. To decrease this risk, regularly use a sunscreen with a broad spectrum SPF of 15 or higher and other sun protection measures including:
  - limit time in the sun, expecially from 10 a.m. - 2 p.m.
  - wear long-sleeve shirts, pants, hats, and sunglasses
- Children under 6 months: Ask a doctor

ACTIVE INGREDIENTS:

Titanium Dioxide 11.4%
Zinc Oxide 5.5%

INACTIVE INGREDIENT

OTHER INGREDIENTS:

Water (Deionized)
Caprylic/Capric Triglyceride,

Octyldodecyl Neopentanoate,

VP/Eicosene Copolymer,
Cyclopentasiloxane,

Glyceryl Stearate,
PEG-100 Stearate,

Squalane (Veg. Origin),

Cetyl Alcohol,

Iron Oxides (CI 77491, 77492, 77499)

Dimethicone,

Alumina,
Glycerin,

Olea Europaea (Olive) Fruit Oil,

Persea Gratissima (Avocado) Oil,

Simmondsia Chinensis (Jojoba) Seed Oil,

Tocopheryl Acetate (Natural),

Phenoxyethanol,

Magnesium Aluminum Silicate,

Polyhydroxystearic Acid,

Phenyl Trimethicone,

Citric Acid,

Hexyldecanol,

Ticaxan Xanthan Powder

Cyclomethicone,

Propylene Glycol,

Tocopherol,

Lysine PCA,

Ceramide-3,

Panicum Miliaceum (Millet) Seed Extract,

Ceratonia Siliqua (Carob) Gum,

Phospholipids,

Ruscus Aculeatus Root Extract (Butcherbroom),

Avena Sativa (Oat) Kernel Protein,

Symphytum Officinale Extract (Comfrey),

Plantago Ovata Seed Extract (Plantain),

Hydrolyzed Wheat Protein,

Xanthan Gum,

Trisodium EDTA,

Triethoxycaprylylsilane,

Ethylhexylglycerin,

d-Tocopherol (Vitamin E)

Lysine PCA,

Natural Scent Green Tea,

Cucumber Sage

Sodium Benzoate Powder NF,

Panicum Miliaceum (Millet) Seed Extract,

Ceramide 3,

Cellulose Gum,

Phospholipids,

TEA-Carbomer,

Melon Berry,

Silica,

Avena Sativa (Oat) Kernel Protein,

Sodium Polyacrylate,

Ruscus Aculeatus Root Extract (Butcherbroom),

Symphytum Officinale Rhizome (Comfrey) Root Extract,

Hydrolyzed Wheat Protein,

Plantago Ovata (Plantain) Seed Extract,

Ceratonia Siliqua (Carob) Gum,

Potassium Sorbate,

Proline,

Serine,

Glutamine,

Leucine

WARNINGS:

FOR EXTERNAL USE ONLY

Do not use on damaged or broken skin

When using this product keep oout of eyes. Rinse with water to remove.

Stop use and ask a doctor if rash occurs.

Keep out of reach of children.

Keep out of reach of children. If product is swallowed, get medical help or contact a Poison Control Center right away.

KEEP OUT OF REACH OF CHILDREN. If product is swallowed, get medical help or contact a Poison Control Center right away.